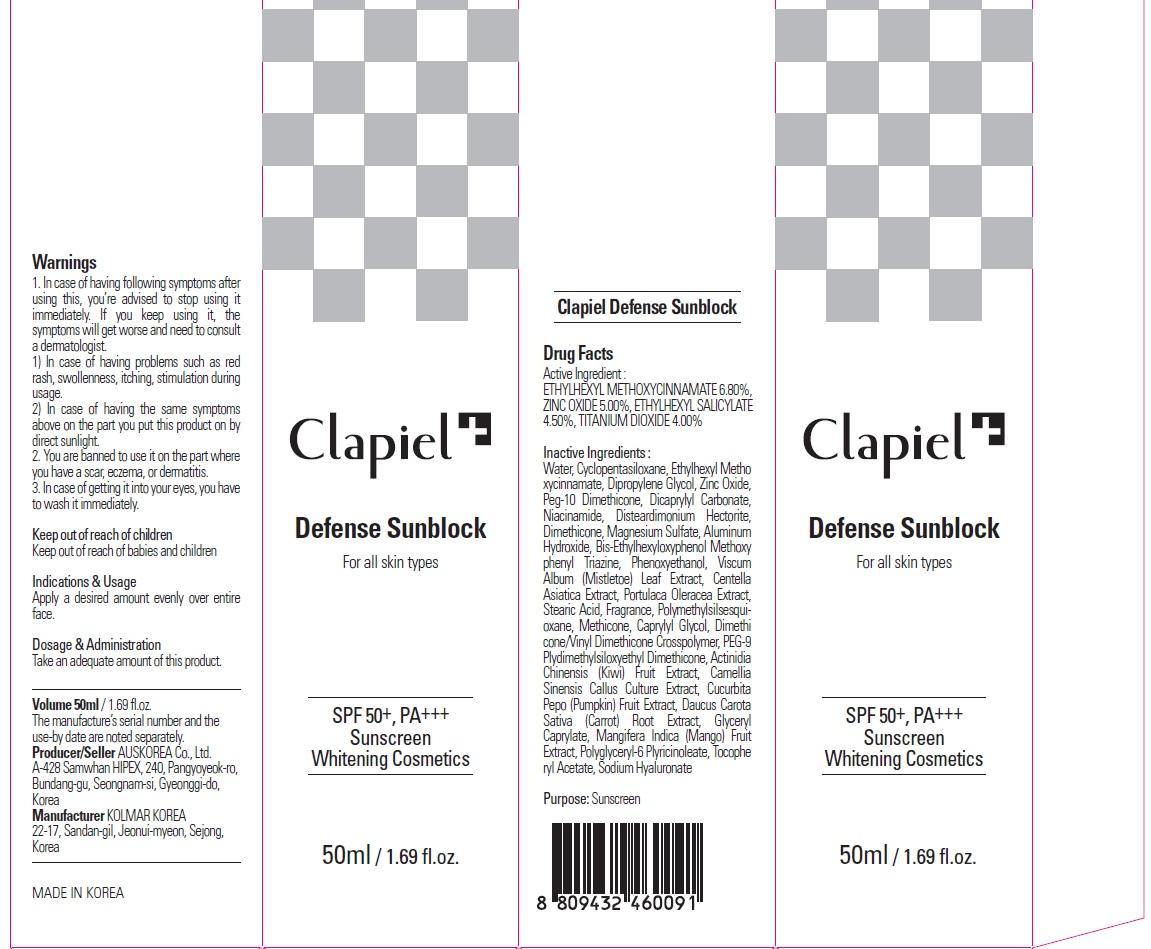 DRUG LABEL: Clapiel Defense Sunblock
NDC: 69977-050 | Form: CREAM
Manufacturer: AUS KOREA CO., LTD.
Category: otc | Type: HUMAN OTC DRUG LABEL
Date: 20150724

ACTIVE INGREDIENTS: OCTINOXATE 3.4 mg/50 mL; ZINC OXIDE 2.5 mg/50 mL; OCTISALATE 2.25 mg/50 mL; TITANIUM DIOXIDE 2.0 mg/50 mL
INACTIVE INGREDIENTS: Water; Dipropylene Glycol

ACTIVE INGREDIENT

Active Ingredient: ETHYLHEXYL METHOXYCINNAMATE 6.80%, ZINC OXIDE 5.00%, ETHYLHEXYL SALICYLATE 4.50%, TITANIUM DIOXIDE 4.00%

INACTIVE INGREDIENT

Inactive Ingredients: Water, Cyclopentasiloxane, Dipropylene Glycol, Peg-10 Dimethicone, Dicaprylyl Carbonate, Niacinamide, Disteardimonium Hectorite, Dimethicone, Magnesium Sulfate, Aluminum Hydroxide, Bis-Ethylhexyloxyphenol Methoxyphenyl Triazine, Phenoxyethanol, Viscum Album (Mistletoe) Leaf Extract, Centella Asiatica Extract, Portulaca Oleracea Extract, Stearic Acid, Fragrance, Polymethylsilsesquioxane, Methicone, Caprylyl Glycol, Dimethicone/Vinyl Dimethicone Crosspolymer, PEG-9 Plydimethylsiloxyethyl Dimethicone, Actinidia Chinensis (Kiwi) Fruit Extract, Camellia Sinensis Callus Culture Extract, Cucurbita Pepo (Pumpkin) Fruit Extract, Daucus Carota Sativa (Carrot) Root Extract, Glyceryl Caprylate, Mangifera Indica (Mango) Fruit Extract, Polyglyceryl-6 Plyricinoleate, Tocopheryl Acetate, Sodium Hyaluronate

PURPOSE

Purpose: Sunscreen

WARNINGS

Warnings: 1. In case of having following symptoms after using this, you’re advised to stop using it immediately. If you keep using it, the symptoms will get worse and need to consult a dermatologist. 1) In case of having problems such as red rash, swollenness, itching, stimulation during usage. 2) In case of having the same symptoms above on the part you put this product on by direct sunlight. 2. You are banned to use it on the part where you have a scar, eczema, or dermatitis. 3. In case of getting it into your eyes, you have to wash it immediately.

Keep out of reach of children: Keep out of reach of babies and children

DESCRIPTION

Indications & Usage: Apply a desired amount evenly over entire face.

Dosage & Administration: Take an adequate amount of this product.